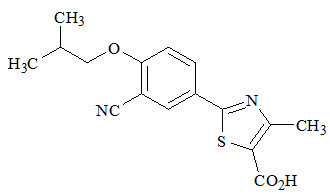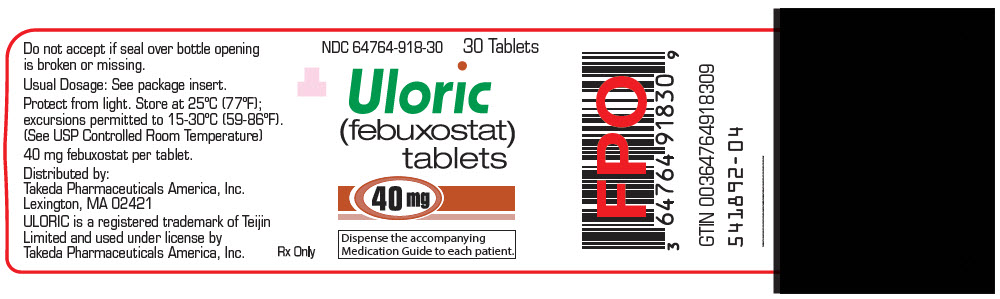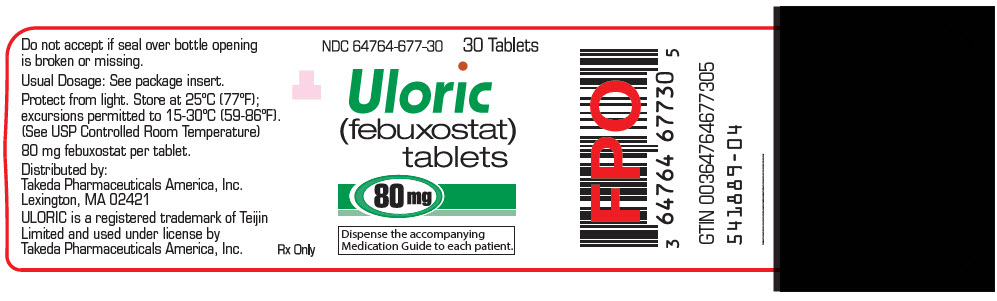 DRUG LABEL: ULORIC
NDC: 64764-918 | Form: TABLET
Manufacturer: Takeda Pharmaceuticals America, Inc.
Category: prescription | Type: HUMAN PRESCRIPTION DRUG LABEL
Date: 20251224

ACTIVE INGREDIENTS: febuxostat 40 mg/1 1
INACTIVE INGREDIENTS: lactose monohydrate; MICROCRYSTALLINE CELLULOSE; HYDROXYPROPYL CELLULOSE (70000 WAMW); croscarmellose sodium; silicon dioxide; magnesium stearate; POLYVINYL ALCOHOL, UNSPECIFIED; Talc; POLYETHYLENE GLYCOL, UNSPECIFIED; Titanium Dioxide; D&C YELLOW NO. 10; FD&C BLUE NO. 1; FD&C BLUE NO. 2

HIGHLIGHTS OF PRESCRIBING INFORMATION

These highlights do not include all the information needed to use ULORIC safely and effectively. See full prescribing information for ULORIC.
ULORIC (febuxostat) tablets, for oral use
Initial U.S. Approval: 2009

WARNING: CARDIOVASCULAR DEATH

See full prescribing information for complete boxed warning.

- Gout patients with established cardiovascular (CV) disease treated with ULORIC had a higher rate of CV death compared to those treated with allopurinol in a CV outcomes study. (5.1)
- Consider the risks and benefits of ULORIC when deciding to prescribe or continue patients on ULORIC. ULORIC should only be used in patients who have an inadequate response to a maximally titrated dose of allopurinol, who are intolerant to allopurinol, or for whom treatment with allopurinol is not advisable. (1)

1 INDICATIONS AND USAGE

ULORIC is a xanthine oxidase (XO) inhibitor indicated for the chronic management of hyperuricemia in adult patients with gout who have an inadequate response to a maximally titrated dose of allopurinol, who are intolerant to allopurinol, or for whom treatment with allopurinol is not advisable. (1)

Limitations of Use:

ULORIC is not recommended for the treatment of asymptomatic hyperuricemia. (1)

2 DOSAGE AND ADMINISTRATION

- Recommended dosage is 40 mg or 80 mg once daily. The recommended starting dosage is 40 mg once daily. For patients who do not achieve a serum uric acid (sUA) less than 6 mg/dL after 2 weeks, the recommended dosage is 80 mg once daily. (2.1)
- Patients with severe renal impairment: Limit the dosage to 40 mg once daily. (2.2, 8.6)
- Flare prophylaxis is recommended upon initiation of ULORIC. (2.4)
- Can be administered without regard to food or antacid use. (2.1)

3 DOSAGE FORMS AND STRENGTHS

Tablet: 40 mg, 80 mg. (3)

4 CONTRAINDICATIONS

ULORIC is contraindicated in patients being treated with azathioprine or mercaptopurine. (4)

5 WARNINGS AND PRECAUTIONS

- Gout Flares: An increase in gout flares is frequently observed after initiation of ULORIC. If a gout flare occurs during treatment, ULORIC need not be discontinued. Prophylactic therapy (i.e., non-steroidal anti-inflammatory drug or colchicine) upon initiation of treatment may be beneficial for up to six months. (2.4, 5.2)
- Hepatic Effects: Cases of hepatic failure, some fatal, have been reported. If liver injury is detected, promptly interrupt ULORIC and treat cause, if possible, to resolution or stabilization. Permanently discontinue ULORIC if liver injury is confirmed, and no alternate etiology can be found. (5.3)
- Serious Skin Reactions: Serious skin and hypersensitivity reactions, including Stevens-Johnson Syndrome, drug reaction with eosinophilia and systemic symptoms and toxic epidermal necrolysis have been reported in patients taking ULORIC. Discontinue ULORIC if serious skin reactions are suspected. (5.4)

6 ADVERSE REACTIONS

Adverse reactions in ≥ 1% of patients treated with ULORIC are liver function abnormalities, nausea, arthralgia, and rash. (6.1)

To report SUSPECTED ADVERSE REACTIONS, contact Takeda Pharmaceuticals America, Inc. at 1-877-TAKEDA-7 (1-877-825-3327) or FDA at 1-800-FDA-1088 or www.fda.gov/medwatch.

7 DRUG INTERACTIONS

Concomitant administration of ULORIC with XO substrate drugs, azathioprine or mercaptopurine could increase plasma concentrations of these drugs resulting in severe toxicity. (7)

8 USE IN SPECIFIC POPULATIONS

- Patients with severe hepatic impairment: No studies have been conducted in this patient population. Caution should be exercised in these patients. (8.7)
- Patients with secondary hyperuricemia (including patients being treated for Lesch-Nyhan syndrome or malignant disease, or in organ transplant recipients): ULORIC is not recommended for use as no studies have been conducted in this patient population. (8.8)

FULL PRESCRIBING INFORMATION

WARNING: CARDIOVASCULAR DEATH

Gout patients with established cardiovascular (CV) disease treated with ULORIC had a higher rate of CV death compared to those treated with allopurinol in a CV outcomes study [see Warnings and Precautions (5.1)].

Consider the risks and benefits of ULORIC when deciding to prescribe or continue patients on ULORIC. ULORIC should only be used in patients who have an inadequate response to a maximally titrated dose of allopurinol, who are intolerant to allopurinol, or for whom treatment with allopurinol is not advisable [see Indications and Usage (1)].

1 INDICATIONS AND USAGE

ULORIC is a xanthine oxidase (XO) inhibitor indicated for the chronic management of hyperuricemia in adult patients with gout who have an inadequate response to a maximally titrated dose of allopurinol, who are intolerant to allopurinol, or for whom treatment with allopurinol is not advisable.

Limitations of Use:

ULORIC is not recommended for the treatment of asymptomatic hyperuricemia.

2 DOSAGE AND ADMINISTRATION

2.1 Recommended Dosage

The recommended ULORIC dosage is 40 mg or 80 mg once daily.

The recommended starting dosage of ULORIC is 40 mg once daily. For patients who do not achieve a serum uric acid (sUA) less than 6 mg/dL after two weeks, the recommended ULORIC dosage is 80 mg once daily.

ULORIC can be taken without regard to food or antacid use [see Clinical Pharmacology (12.3)].

Concurrent prophylactic treatment with a non-steroidal anti-inflammatory drug (NSAID) or colchicine is recommended [see Dosage and Administration (2.4) and Warnings and Precautions (5.2)].

2.2 Dosage Recommendations in Patients with Renal Impairment and Hepatic Impairment

The recommended dosage of ULORIC is limited to 40 mg once daily in patients with severe renal impairment. No dose modification is necessary when administering ULORIC in patients with mild or moderate renal impairment [see Use in Specific Populations (8.6) and Clinical Pharmacology (12.3)].

No dosage modification is necessary in patients with mild to moderate hepatic impairment [see Use in Specific Populations (8.7) and Clinical Pharmacology (12.3)].

2.3 Serum Uric Acid Level Monitoring

Testing for the target serum uric acid level of less than 6 mg/dL may be performed as early as two weeks after initiating ULORIC therapy.

2.4 Recommended Prophylaxis for Gout Flares

Gout flares may occur after initiation of ULORIC due to changing serum uric acid levels resulting in mobilization of urate from tissue deposits. Flare prophylaxis with a non-steroidal anti-inflammatory drug (NSAID) or colchicine is recommended upon initiation of ULORIC. Prophylactic therapy may be beneficial for up to six months [see Clinical Studies (14.1)].

If a gout flare occurs during ULORIC treatment, ULORIC need not be discontinued. The gout flare should be managed concurrently, as appropriate for the individual patient [see Warnings and Precautions (5.2)].

3 DOSAGE FORMS AND STRENGTHS

- 40 mg tablets, light green to green, round, debossed with "TAP" and "40"
- 80 mg tablets, light green to green, teardrop shaped, debossed with "TAP" and "80"

4 CONTRAINDICATIONS

ULORIC is contraindicated in patients being treated with azathioprine or mercaptopurine [see Drug Interactions (7)].

5 WARNINGS AND PRECAUTIONS

5.1 Cardiovascular Death

In a cardiovascular (CV) outcome study, gout patients with established CV disease treated with ULORIC had a higher rate of CV death compared to those treated with allopurinol. Sudden cardiac death was the most common cause of adjudicated CV deaths, 2.7% in the ULORIC group (83 of 3,098) as compared to 1.8% in the allopurinol group (56 of 3,092). ULORIC was similar to allopurinol for nonfatal myocardial infarction (MI), nonfatal stroke and unstable angina with urgent coronary revascularization [see Clinical Studies (14.2)].

Because of the increased risk of CV death, ULORIC should only be used in patients who have an inadequate response to a maximally titrated dose of allopurinol, who are intolerant to allopurinol, or for whom treatment with allopurinol is not advisable [see Indications and Usage(1)].

Consider the risks and benefits of ULORIC when deciding to prescribe or continue patients on ULORIC. Consider use of prophylactic low-dose aspirin therapy in patients with a history of CV disease. Monitor patients for the development of CV events. Inform patients about the symptoms of serious CV events and the steps to take if they occur.

5.2 Gout Flares

After initiation of ULORIC, an increase in gout flares is frequently observed. This increase is due to reduction in serum uric acid levels, resulting in mobilization of urate from tissue deposits.

In order to prevent gout flares when ULORIC is initiated, concurrent prophylactic treatment with an NSAID or colchicine is recommended [see Dosage and Administration (2.4)].

5.3 Hepatic Effects

Cases of fatal and nonfatal hepatic failure in patients taking ULORIC have been reported. During randomized controlled studies, transaminase elevations greater than three times the upper limit of normal (ULN) were observed (AST: 2%, 2%, and ALT: 3%, 2% in ULORIC and allopurinol-treated patients, respectively). No dose-effect relationship for these transaminase elevations was noted [see Clinical Pharmacology (12.3)].

Obtain a liver test panel (serum alanine aminotransferase [ALT], aspartate aminotransferase [AST], alkaline phosphatase, and total bilirubin) as a baseline before initiating ULORIC.

Measure liver tests promptly in patients who report symptoms that may indicate liver injury, including fatigue, anorexia, right upper abdominal discomfort, dark urine or jaundice. In this clinical context, if the patient presents abnormal liver tests (ALT or AST greater than three times the upper limit of the reference range), interrupt ULORIC treatment while investigating the probable cause. Permanently discontinue ULORIC if liver injury is confirmed, and no alternate etiology can be found.

Permanently discontinue ULORIC in patients who have serum ALT or AST greater than three times the reference range with serum total bilirubin greater than two times the reference range without alternative etiologies because they are at risk for severe drug-induced liver injury. For patients with lesser elevations of serum ALT or bilirubin and with an alternate probable cause, treatment with ULORIC can be used with close monitoring.

5.4 Serious Skin Reactions

Serious skin and hypersensitivity reactions, including Stevens-Johnson Syndrome, drug reaction with eosinophilia and systemic symptoms (DRESS) and toxic epidermal necrolysis (TEN) have been reported postmarketing in patients taking ULORIC. Discontinue ULORIC if serious skin reactions are suspected [see Patient Counseling Information (17)]. Many of these patients had reported previous similar skin reactions to allopurinol. ULORIC should be used with close monitoring in these patients.

6 ADVERSE REACTIONS

The following serious adverse reactions are described elsewhere in the prescribing information:

- Cardiovascular Death [see Warnings and Precautions (5.1)]
- Hepatic Effects [see Warnings and Precautions (5.3)]
- Serious Skin Reactions [see Warnings and Precautions (5.4)]

6.1 Clinical Trials Experience

Because clinical trials are conducted under widely varying conditions, adverse reaction rates observed in the clinical trials of a drug cannot be directly compared to rates in the clinical trials of another drug and may not reflect the rates observed in practice.

In Phase 2 and 3 clinical studies, a total of 2757 patients with hyperuricemia and gout were treated with ULORIC 40 mg or 80 mg daily. For ULORIC 40 mg, 559 patients were treated for ≥6 months. For ULORIC 80 mg, 1377 patients were treated for ≥6 months, 674 patients were treated for ≥1 year and 515 patients were treated for ≥2 years. In the CARES study, a total of 3098 patients were treated with ULORIC 40 mg or 80 mg daily; of these, 2155 patients were treated for ≥1 year and 1539 were treated for ≥2 years [see Clinical Studies (14.2)].

Most Common Adverse Reactions

In three randomized, controlled clinical studies (Studies 1, 2 and 3), which were 6 to 12 months in duration, the following adverse reactions were reported by the treating physician as related to study drug. Table 1 summarizes adverse reactions reported at a rate of at least 1% in ULORIC treatment groups and at least 0.5% greater than placebo.

Table 1: Adverse Reactions Occurring in ≥1% of Patients Treated with ULORIC and at Least 0.5% Greater than in Patients Receiving Placebo in Controlled Studies
 | Placebo | ULORIC |  | allopurinol [Of the patients who received allopurinol, 10 received 100 mg, 145 received 200 mg, and 1122 received 300 mg, based on level of renal impairment.]
Adverse Reactions | (N=134) | 40 mg daily (N=757) | 80 mg daily (N=1279) | (N=1277)
Liver Function Abnormalities | 0.7% | 6.6% | 4.6% | 4.2%
Nausea | 0.7% | 1.1% | 1.3% | 0.8%
Arthralgia | 0% | 1.1% | 0.7% | 0.7%
Rash | 0.7% | 0.5% | 1.6% | 1.6%

The most common adverse reaction leading to discontinuation from therapy was liver function abnormalities in 1.8% of ULORIC 40 mg, 1.2% of ULORIC 80 mg, and in 0.9% of patients treated with allopurinol.

In addition to the adverse reactions presented in Table 1, dizziness was reported in more than 1% of patients treated with ULORIC although not at a rate more than 0.5% greater than placebo.

In the CARES study, liver function abnormalities and diarrhea were reported in more than 1% of patients treated with ULORIC, although not at a rate more than 0.5% greater than allopurinol.

Less Common Adverse Reactions

In clinical studies the following adverse reactions occurred in less than 1% of patients and in more than one subject treated with doses ranging from 40 mg to 240 mg of ULORIC. This list also includes adverse reactions (less than 1% of patients) associated with organ systems from Warnings and Precautions.

Blood and Lymphatic System Disorders: anemia, idiopathic thrombocytopenic purpura, leukocytosis/leukopenia, neutropenia, pancytopenia, splenomegaly, thrombocytopenia.

Cardiac Disorders: angina pectoris, atrial fibrillation/flutter, cardiac murmur, ECG abnormal, palpitations, sinus bradycardia, tachycardia.

Ear and Labyrinth Disorders: deafness, tinnitus, vertigo.

Eye Disorders: vision blurred.

Gastrointestinal Disorders: abdominal distention, abdominal pain, constipation, dry mouth, dyspepsia, flatulence, frequent stools, gastritis, gastroesophageal reflux disease, gastrointestinal discomfort, gingival pain, hematemesis, hyperchlorhydria, hematochezia, mouth ulceration, pancreatitis, peptic ulcer, vomiting.

General Disorders and Administration Site Conditions: asthenia, chest pain/discomfort, edema, fatigue, feeling abnormal, gait disturbance, influenza-like symptoms, mass, pain, thirst.

Hepatobiliary Disorders: cholelithiasis/cholecystitis, hepatic steatosis, hepatitis, hepatomegaly.

Immune System Disorder: hypersensitivity.

Infections and Infestations: herpes zoster.

Procedural Complications: contusion.

Metabolism and Nutrition Disorders: anorexia, appetite decreased/increased, dehydration, diabetes mellitus, hypercholesterolemia, hyperglycemia, hyperlipidemia, hypertriglyceridemia, hypokalemia, weight decreased/increased.

Musculoskeletal and Connective Tissue Disorders: arthritis, joint stiffness, joint swelling, muscle spasms/twitching/tightness/weakness, musculoskeletal pain/stiffness, myalgia.

Nervous System Disorders: altered taste, balance disorder, cerebrovascular accident, Guillain-Barré syndrome, headache, hemiparesis, hypoesthesia, hyposmia, lacunar infarction, lethargy, mental impairment, migraine, paresthesia, somnolence, transient ischemic attack, tremor.

Psychiatric Disorders: agitation, anxiety, depression, insomnia, irritability, libido decreased, nervousness, panic attack, personality change.

Renal and Urinary Disorders: hematuria, nephrolithiasis, pollakiuria, proteinuria, renal failure, renal insufficiency, urgency, incontinence.

Reproductive System and Breast Changes: breast pain, erectile dysfunction, gynecomastia.

Respiratory, Thoracic and Mediastinal Disorders: bronchitis, cough, dyspnea, epistaxis, nasal dryness, paranasal sinus hypersecretion, pharyngeal edema, respiratory tract congestion, sneezing, throat irritation, upper respiratory tract infection.

Skin and Subcutaneous Tissue Disorders: alopecia, angio edema, dermatitis, dermographism, ecchymosis, eczema, hair color changes, hair growth abnormal, hyperhidrosis, peeling skin, petechiae, photosensitivity, pruritus, purpura, skin discoloration/altered pigmentation, skin lesion, skin odor abnormal, urticaria.

Vascular Disorders: flushing, hot flush, hypertension, hypotension.

Laboratory Parameters: activated partial thromboplastin time prolonged, creatine increased, bicarbonate decreased, sodium increased, EEG abnormal, glucose increased, cholesterol increased, triglycerides increased, amylase increased, potassium increased, TSH increased, platelet count decreased, hematocrit decreased, hemoglobin decreased, MCV increased, RBC decreased, creatinine increased, blood urea increased, BUN/creatinine ratio increased, creatine phosphokinase (CPK) increased, alkaline phosphatase increased, LDH increased, PSA increased, urine output increased/decreased, lymphocyte count decreased, neutrophil count decreased, WBC increased/decreased, coagulation test abnormal, low density lipoprotein (LDL) increased, prothrombin time prolonged, urinary casts, urine positive for white blood cells and protein.

6.2 Postmarketing Experience

The following adverse reactions have been identified during post approval use of ULORIC. Because these reactions are reported voluntarily from a population of uncertain size, it is not always possible to reliably estimate their frequency or establish a causal relationship to drug exposure.

Blood and Lymphatic System Disorders: agranulocytosis, eosinophilia.

Hepatobiliary Disorders: hepatic failure (some fatal), jaundice, serious cases of abnormal liver function test results, liver disorder.

Immune System Disorders: anaphylaxis, anaphylactic reaction.

Musculoskeletal and Connective Tissue Disorders: rhabdomyolysis.

Psychiatric Disorders: psychotic behavior including aggressive thoughts.

Renal and Urinary Disorders: tubulointerstitial nephritis.

Skin and Subcutaneous Tissue Disorders: generalized rash, Stevens-Johnson Syndrome, hypersensitivity skin reactions, erythema multiforme, drug reaction with eosinophilia and systemic symptoms, toxic epidermal necrolysis.

7 DRUG INTERACTIONS

7.1 Xanthine Oxidase Substrate Drugs

ULORIC is an XO inhibitor. Based on a drug interaction study in healthy patients, febuxostat altered the metabolism of theophylline (a substrate of XO) in humans [see Clinical Pharmacology (12.3)]. Therefore, use with caution when coadministering ULORIC with theophylline.

A drug interaction study of ULORIC and azathioprine, also metabolized by XO, showed an increase in exposure of 6-mercaptopurine which may lead to toxicity [see Clinical Pharmacology (12.3)]. Drug interaction studies of ULORIC with other drugs that are metabolized by XO (e.g., mercaptopurine) have not been conducted. ULORIC is contraindicated in patients being treated with azathioprine or mercaptopurine [see Contraindications (4)].

7.2 Cytotoxic Chemotherapy Drugs

Drug interaction studies of ULORIC with cytotoxic chemotherapy have not been conducted. No data are available regarding the safety of ULORIC during cytotoxic chemotherapy.

7.3 In Vivo Drug Interaction Studies

Based on drug interaction studies in healthy patients, ULORIC does not have clinically significant interactions with colchicine, naproxen, indomethacin, hydrochlorothiazide, warfarin or desipramine [see Clinical Pharmacology (12.3)]. Therefore, ULORIC may be used concomitantly with these medications.

8 USE IN SPECIFIC POPULATIONS

8.1 Pregnancy

Risk Summary

Limited available data with ULORIC use in pregnant women are insufficient to inform a drug associated risk of adverse developmental outcomes. No adverse developmental effects were observed in embryo-fetal development studies with oral administration of febuxostat to pregnant rats and rabbits during organogenesis at doses that produced maternal exposures up to 40 and 51 times, respectively, the exposure at the maximum recommended human dose (MRHD). No adverse developmental effects were observed in a pre- and postnatal development study with administration of febuxostat to pregnant rats from organogenesis through lactation at an exposure approximately 11 times the MRHD (see Data).

The estimated background risk of major birth defects and miscarriage for the indicated population is unknown. All pregnancies have a background risk of birth defect, loss, or other adverse outcomes. In the US general population, the estimated background risk of major birth defects and miscarriage in clinically recognized pregnancies is 2 to 4% and 15 to 20%, respectively.

Data

Animal Data

In an embryo-fetal development study in pregnant rats dosed during the period of organogenesis from gestation Days 7 – 17, febuxostat was not teratogenic and did not affect fetal development or survival at exposures up to approximately 40 times the MRHD (on an AUC basis at maternal oral doses up to 48 mg/kg/day). In an embryo-fetal development study in pregnant rabbits dosed during the period of organogenesis from gestation Days 6 – 18, febuxostat was not teratogenic and did not affect fetal development at exposures up to approximately 51 times the MRHD (on an AUC basis at maternal oral doses up to 48 mg/kg/day).

In a pre- and postnatal development study in pregnant female rats dosed orally from gestation Day 7 through lactation Day 20, febuxostat had no effects on delivery or growth and development of offspring at a dose approximately 11 times the MRHD (on an AUC basis at a maternal oral dose of 12 mg/kg/day). However, increased neonatal mortality and a reduction in neonatal body weight gain were observed in the presence of maternal toxicity at a dose approximately 40 times the MRHD (on an AUC basis at a maternal oral dose of 48 mg/kg/day).

Febuxostat crossed the placental barrier following oral administration to pregnant rats and was detected in fetal tissues.

8.2 Lactation

Risk Summary

There are no data on the presence of febuxostat in human milk, the effects on the breastfed infant, or the effects on milk production. Febuxostat is present in rat milk. The developmental and health benefits of breastfeeding should be considered along with the mother's clinical need for ULORIC and any potential adverse effects on the breastfed child from ULORIC or from the underlying maternal condition.

Data

Animal Data

Orally administered febuxostat was detected in the milk of lactating rats at up to approximately 7 times the plasma concentration.

8.4 Pediatric Use

Safety and effectiveness of ULORIC in pediatric patients have not been established.

8.5 Geriatric Use

No dose adjustment is necessary in elderly patients. Of the total number of patients in Studies 1, 2, and 3 (clinical studies of ULORIC in the treatment of gout) [see Clinical Studies (14.1)], 16% were 65 and over, while 4% were 75 and over. Comparing patients in different age groups, no clinically significant differences in safety or effectiveness were observed but greater sensitivity of some older individuals cannot be ruled out. The Cmax and AUC24 of febuxostat following multiple oral doses of ULORIC in geriatric patients (≥65 years) were similar to those in younger patients (18 to 40 years) [see Clinical Pharmacology (12.3)].

8.6 Renal Impairment

No dose adjustment is necessary in patients with mild to moderate renal impairment (Clcr 30 to 89 mL/min). For patients with severe renal impairment (Clcr 15 to 29 mL/min), the recommended dosage of ULORIC is limited to 40 mg once daily [see Dosage and Administration (2.2) and Clinical Pharmacology (12.3)].

8.7 Hepatic Impairment

No dose adjustment is necessary in patients with mild or moderate hepatic impairment (Child-Pugh Class A or B). No studies have been conducted in patients with severe hepatic impairment (Child-Pugh Class C); therefore, caution should be exercised in these patients [see Clinical Pharmacology (12.3)].

8.8 Secondary Hyperuricemia

No studies have been conducted in patients with secondary hyperuricemia (including organ transplant recipients); ULORIC is not recommended for use in patients whom the rate of urate formation is greatly increased (e.g., malignant disease and its treatment, Lesch-Nyhan syndrome). The concentration of xanthine in urine could, in rare cases, rise sufficiently to allow deposition in the urinary tract.

10 OVERDOSAGE

ULORIC was studied in healthy patients in doses up to 300 mg daily for seven days without evidence of dose-limiting toxicities. No overdose of ULORIC was reported in clinical studies. Patients should be managed by symptomatic and supportive care should there be an overdose.

11 DESCRIPTION

ULORIC (febuxostat) is a xanthine oxidase inhibitor. The active ingredient in ULORIC is 2-[3-cyano-4-(2-methylpropoxy) phenyl]-4-methylthiazole-5-carboxylic acid, with a molecular weight of 316.38. The empirical formula is C16H16N2O3S.

The chemical structure is:

Febuxostat is a non-hygroscopic, white crystalline powder that is freely soluble in dimethylformamide; soluble in dimethylsulfoxide; sparingly soluble in ethanol; slightly soluble in methanol and acetonitrile; and practically insoluble in water. The melting range is 205°C to 208°C.

ULORIC tablets for oral use contain the active ingredient, febuxostat, and are available in two dosage strengths, 40 mg and 80 mg. Inactive ingredients include hydroxypropyl cellulose, lactose monohydrate, magnesium stearate, microcrystalline cellulose, silicon dioxide, and sodium croscarmellose. ULORIC tablets are coated with Opadry II, green.

12 CLINICAL PHARMACOLOGY

12.1 Mechanism of Action

ULORIC, a xanthine oxidase inhibitor, achieves its therapeutic effect by decreasing serum uric acid. ULORIC is not expected to inhibit other enzymes involved in purine and pyrimidine synthesis and metabolism at therapeutic concentrations.

12.2 Pharmacodynamics

Effect on Uric Acid and Xanthine Concentrations

In healthy patients, ULORIC resulted in a dose dependent decrease in 24-hour mean serum uric acid concentrations and an increase in 24-hour mean serum xanthine concentrations. In addition, there was a decrease in the total daily urinary uric acid excretion. Also, there was an increase in total daily urinary xanthine excretion. Percent reduction in 24-hour mean serum uric acid concentrations was between 40% and 55% at the exposure levels of 40 mg and 80 mg daily doses.

Effect on Cardiac Repolarization

The effect of ULORIC on cardiac repolarization as assessed by the QTc interval was evaluated in normal healthy patients and in patients with gout. ULORIC in doses up to 300 mg daily (3.75 times the maximum recommended daily dosage), at steady-state, did not demonstrate an effect on the QTc interval.

12.3 Pharmacokinetics

In healthy patients, maximum plasma concentrations (Cmax) and AUC of febuxostat increased in a dose proportional manner following single and multiple doses of 10 mg (0.25 times the lowest recommended dosage) to 120 mg (1.5 times the maximum recommended dosage). There is no accumulation when therapeutic doses are administered every 24 hours. Febuxostat has an apparent mean terminal elimination half-life (t1/2) of approximately 5 to 8 hours. Febuxostat pharmacokinetic parameters for patients with hyperuricemia and gout estimated by population pharmacokinetic analyses were similar to those estimated in healthy patients.

Absorption

The absorption of radiolabeled febuxostat following oral dose administration was estimated to be at least 49% (based on total radioactivity recovered in urine). Maximum plasma concentrations of febuxostat occurred between 1 and 1.5 hours postdose. After multiple oral 40 mg and 80 mg once daily doses, Cmax is approximately 1.6 ± 0.6 mcg/mL (N=30), and 2.6 ± 1.7 mcg/mL (N=227), respectively. Absolute bioavailability of the febuxostat tablet has not been studied.

Following multiple 80 mg once daily doses with a high fat meal, there was a 49% decrease in Cmax and an 18% decrease in AUC, respectively. However, no clinically significant change in the percent decrease in serum uric acid concentration was observed (58% fed vs 51% fasting). Thus, ULORIC may be taken without regard to food.

Concomitant ingestion of an antacid containing magnesium hydroxide and aluminum hydroxide with an 80 mg single dose of ULORIC has been shown to delay absorption of febuxostat (approximately one hour) and to cause a 31% decrease in Cmax and a 15% decrease in AUC∞. As AUC rather than Cmax was related to drug effect, change observed in AUC was not considered clinically significant. Therefore, ULORIC may be taken without regard to antacid use.

Distribution

The mean apparent steady state volume of distribution (Vss/F) of febuxostat was approximately 50 L (CV ~40%). The plasma protein binding of febuxostat is approximately 99.2% (primarily to albumin), and is constant over the concentration range achieved with 40 mg and 80 mg doses.

Metabolism

Febuxostat is extensively metabolized by both conjugation via uridine diphosphate glucuronosyltransferase (UGT) enzymes including UGT1A1, UGT1A3, UGT1A9, and UGT2B7 and oxidation via cytochrome P450 (CYP) enzymes including CYP1A2, 2C8 and 2C9 and non-P450 enzymes. The relative contribution of each enzyme isoform in the metabolism of febuxostat is not clear. The oxidation of the isobutyl side chain leads to the formation of four pharmacologically active hydroxy metabolites, all of which occur in plasma of humans at a much lower extent than febuxostat.

In urine and feces, acyl glucuronide metabolites of febuxostat (~35% of the dose), and oxidative metabolites, 67M-1 (~10% of the dose), 67M-2 (~11% of the dose), and 67M-4, a secondary metabolite from 67M-1 (~14% of the dose), appeared to be the major metabolites of febuxostat in vivo.

Elimination

Febuxostat is eliminated by both hepatic and renal pathways. Following an 80 mg oral dose of ^14C-labeled febuxostat, approximately 49% of the dose was recovered in the urine as unchanged febuxostat (3%), the acyl glucuronide of the drug (30%), its known oxidative metabolites and their conjugates (13%), and other unknown metabolites (3%). In addition to the urinary excretion, approximately 45% of the dose was recovered in the feces as the unchanged febuxostat (12%), the acyl glucuronide of the drug (1%), its known oxidative metabolites and their conjugates (25%), and other unknown metabolites (7%).

The apparent mean terminal elimination half-life (t1/2) of febuxostat was approximately 5 to 8 hours.

Specific Populations

Geriatric Patients

The Cmax and AUC of febuxostat and its metabolites following multiple oral doses of ULORIC in geriatric patients (≥65 years) were similar to those in younger patients (18 to 40 years). In addition, the percent decrease in serum uric acid concentration was similar between elderly and younger patients. No dose adjustment is necessary in geriatric patients [see Use in Specific Populations (8.5)].

Patients with Renal Impairment

In a dedicated phase I pharmacokinetics study, following multiple 80 mg doses of ULORIC in healthy patients with mild (Clcr 50 to 80 mL/min), moderate (Clcr 30 to 49 mL/min) or severe renal impairment (Clcr 10 to 29 mL/min), the Cmax of febuxostat did not change relative to patients with normal renal function (Clcr greater than 80 mL/min). AUC and half-life of febuxostat increased in patients with renal impairment in comparison to patients with normal renal function, but values were similar among three renal impairment groups. Mean febuxostat AUC values were up to 1.8 times higher in patients with renal impairment compared to those with normal renal function. Mean Cmax and AUC values for three active metabolites increased up to two and four-fold, respectively. However, the percent decrease in serum uric acid concentration for patients with renal impairment was comparable to those with normal renal function (58% in normal renal function group and 55% in the severe renal function group).

Based on population pharmacokinetic analysis, following multiple 40 mg or 80 mg doses of ULORIC, the mean oral clearance (CL/F) values of febuxostat in patients with gout and mild (n=334), moderate (n=232) or severe (n=34) renal impairment were decreased by 14%, 34%, and 48%, respectively, compared to patients with normal (n=89) renal function. The corresponding median AUC values of febuxostat at steady-state in patients with renal impairment were increased by 18%, 49%, and 96% after 40 mg dose, and 7%, 45% and 98% after 80 mg dose, respectively, compared to patients with normal renal function.

ULORIC has not been studied in end stage renal impairment patients who are on dialysis.

Patients with Hepatic Impairment

Following multiple 80 mg doses of ULORIC in patients with mild (Child-Pugh Class A) or moderate (Child-Pugh Class B) hepatic impairment, an average of 20% to 30% increase was observed for both Cmax and AUC24 (total and unbound) in hepatic impairment groups compared to patients with normal hepatic function. In addition, the percent decrease in serum uric acid concentration was comparable between different hepatic groups (62% in healthy group, 49% in mild hepatic impairment group, and 48% in moderate hepatic impairment group). No dose adjustment is necessary in patients with mild or moderate hepatic impairment. No studies have been conducted in patients with severe hepatic impairment (Child-Pugh Class C); caution should be exercised in those patients [see Use in Specific Populations (8.7)].

Male and Female Patients

Following multiple oral doses of ULORIC, the Cmax and AUC24 of febuxostat were 30% and 14% higher in females than in males, respectively. However, weight-corrected Cmax and AUC were similar between the genders. In addition, the percent decrease in serum uric acid concentrations was similar between genders. No dose adjustment is necessary based on gender.

Racial Groups

No specific pharmacokinetic study was conducted to investigate the effects of race.

Drug Interaction Studies

Effect of ULORIC on Other Drugs

Xanthine Oxidase Substrate Drugs-Azathioprine, Mercaptopurine, and Theophylline

Febuxostat is an XO inhibitor. A drug-drug interaction study evaluating the effect of ULORIC upon the pharmacokinetics of theophylline (an XO substrate) in healthy patients showed that coadministration of febuxostat with theophylline resulted in an approximately 400-fold increase in the amount of 1-methylxanthine, one of the major metabolites of theophylline, excreted in the urine. Since the long-term safety of exposure to 1-methylxanthine in humans is unknown, use with caution when coadministering febuxostat with theophylline.

A drug interaction study of ULORIC and azathioprine has been conducted [see Drug Interactions (7)]. Inhibition of XO by ULORIC caused increased plasma concentrations of 6-mercaptopurine, a metabolite of azathioprine, which may lead to toxicity. Drug interaction studies of ULORIC with other drugs that are metabolized by XO (e.g., mercaptopurine) have not been conducted. ULORIC is contraindicated in patients being treated with azathioprine or mercaptopurine [see Contraindications (4) and Drug Interactions (7)].

Azathioprine and mercaptopurine undergo metabolism via three major metabolic pathways, one of which is mediated by XO. Concomitant administration of allopurinol [a xanthine oxidase inhibitor] with azathioprine or mercaptopurine has been reported to substantially increase plasma concentrations of these drugs. Because ULORIC is a xanthine oxidase inhibitor, it could inhibit the XO-mediated metabolism of mercaptopurine leading to increased plasma concentrations of mercaptopurine that could result in severe toxicity.

P450 Substrate Drugs

In vitro studies have shown that febuxostat does not inhibit P450 enzymes CYP1A2, 2C9, 2C19, 2D6, or 3A4 and it also does not induce CYP1A2, 2B6, 2C9, 2C19, or 3A4 at clinically relevant concentrations. As such, pharmacokinetic interactions between ULORIC and drugs metabolized by these CYP enzymes are unlikely.

Effect of Other Drugs on ULORIC

Febuxostat is metabolized by conjugation and oxidation via multiple metabolizing enzymes. The relative contribution of each enzyme isoform is not clear. Drug interactions between ULORIC and a drug that inhibits or induces one particular enzyme isoform is in general not expected.

In Vivo Drug Interaction Studies

Azathioprine

Concomitant use of ULORIC and azathioprine is contraindicated. Coadministration with febuxostat (40 mg or 120 mg QD) reduced the apparent clearance of mercaptopurine, a XO substrate, by 83.2% to 83.8% following a single oral dose of azathioprine, a prodrug of 6-mercaptopurine. No significant differences were observed in the extent of inhibition of 6-mercaptopurine metabolism by febuxostat 40 mg and 120 mg.

Theophylline

No dose adjustment is necessary for theophylline when coadministered with ULORIC. Administration of ULORIC (80 mg once daily) with theophylline resulted in an increase of 6% in Cmax and 6.5% in AUC of theophylline. These changes were not considered statistically significant. However, the study also showed an approximately 400-fold increase in the amount of 1-methylxanthine (one of the major theophylline metabolites) excreted in urine as a result of XO inhibition by ULORIC. The safety of long-term exposure to 1-methylxanthine has not been evaluated. This should be taken into consideration when deciding to coadminister ULORIC and theophylline.

Colchicine

No dose adjustment is necessary for either ULORIC or colchicine when the two drugs are coadministered. Administration of ULORIC (40 mg once daily) with colchicine (0.6 mg twice daily) resulted in an increase of 12% in Cmax and 7% in AUC24 of febuxostat. In addition, administration of colchicine (0.6 mg twice daily) with ULORIC (120 mg daily) resulted in a less than 11% change in Cmax or AUC of colchicine for both AM and PM doses. These changes were not considered clinically significant.

Naproxen

No dose adjustment is necessary for ULORIC or naproxen when the two drugs are coadministered. Administration of ULORIC (80 mg once daily) with naproxen (500 mg twice daily) resulted in a 28% increase in Cmax and a 40% increase in AUC of febuxostat. The increases were not considered clinically significant. In addition, there were no significant changes in the Cmax or AUC of naproxen (less than 2%).

Indomethacin

No dose adjustment is necessary for either ULORIC or indomethacin when these two drugs are coadministered. Administration of ULORIC (80 mg once daily) with indomethacin (50 mg twice daily) did not result in any significant changes in Cmax or AUC of febuxostat or indomethacin (less than 7%).

Hydrochlorothiazide

No dose adjustment is necessary for ULORIC when coadministered with hydrochlorothiazide. Administration of ULORIC (80 mg) with hydrochlorothiazide (50 mg) did not result in any clinically significant changes in Cmax or AUC of febuxostat (less than 4%), and serum uric acid concentrations were not substantially affected.

Warfarin

No dose adjustment is necessary for warfarin when coadministered with ULORIC. Administration of ULORIC (80 mg once daily) with warfarin had no effect on the pharmacokinetics of warfarin in healthy patients. INR and Factor VII activity were also not affected by the coadministration of ULORIC.

Desipramine

Coadministration of drugs that are CYP2D6 substrates (such as desipramine) with ULORIC are not expected to require dose adjustment. Febuxostat was shown to be a weak inhibitor of CYP2D6 in vitro and in vivo. Administration of ULORIC (120 mg once daily) with desipramine (25 mg) resulted in an increase in Cmax (16%) and AUC (22%) of desipramine, which was associated with a 17% decrease in the 2-hydroxydesipramine to desipramine metabolic ratio (based on AUC).

13 NONCLINICAL TOXICOLOGY

13.1 Carcinogenesis, Mutagenesis, Impairment of Fertility

Two-year carcinogenicity studies were conducted in F344 rats and B6C3F1 mice. Increased transitional cell papilloma and carcinoma of the urinary bladder was observed at 24 mg/kg (25 times the MRHD on an AUC basis and 18.75 mg/kg (12.5 times the MRHD on an AUC basis) in male rats and female mice, respectively. The urinary bladder neoplasms were secondary to calculus formation in the kidney and urinary bladder.

Febuxostat showed a positive clastogenic response in a chromosomal aberration assay in a Chinese hamster lung fibroblast cell line with and without metabolic activation in vitro. Febuxostat was negative in the following genotoxicity assays: the in vitro Ames assay, in vitro chromosomal aberration assay in human peripheral lymphocytes, the L5178Y mouse lymphoma cell line assay, the in vivo mouse micronucleus assay, and the rat unscheduled DNA synthesis assay.

Fertility and reproductive performance were unaffected in male or female rats that received febuxostat at oral doses up to 48 mg/kg/day (approximately 31 and 40 times the MRHD on an AUC basis in males and females respectively).

13.2 Animal Toxicology

A 12-month toxicity study in beagle dogs showed deposition of xanthine crystals and calculi in kidneys at 15 mg/kg (approximately 4 times the MRHD on an AUC basis). A similar effect of calculus formation was noted in rats in a 6-month study due to deposition of xanthine crystals at 48 mg/kg (approximately 31 and 40 times the MRHD on an AUC basis in males and females respectively).

14 CLINICAL STUDIES

A serum uric acid level of less than 6 mg/dL is the goal of antihyperuricemic therapy and has been established as appropriate for the treatment of gout.

14.1 Management of Hyperuricemia in Gout

The efficacy of ULORIC was demonstrated in three randomized, double-blind, controlled trials in patients with hyperuricemia and gout. Hyperuricemia was defined as a baseline serum uric acid level ≥8 mg/dL.

Study 1 (NCT00430248) randomized patients to: ULORIC 40 mg daily, ULORIC 80 mg daily, or allopurinol (300 mg daily for patients with estimated creatinine clearance (Clcr) ≥60 mL/min or 200 mg daily for patients with estimated Clcr ≥30 mL/min and ≤59 mL/min). The duration of Study 1 was six months.

Study 2 (NCT00174915) randomized patients to: placebo, ULORIC 80 mg daily, ULORIC 120 mg daily, ULORIC 240 mg daily or allopurinol (300 mg daily for patients with a baseline serum creatinine ≤1.5 mg/dL or 100 mg daily for patients with a baseline serum creatinine greater than 1.5 mg/dL and ≤2 mg/dL). The duration of Study 2 was six months.

Study 3 (NCT00102440), a year study, randomized patients to: ULORIC 80 mg daily, ULORIC 120 mg daily, or allopurinol 300 mg daily. Patients who completed Study 2 and Study 3 were eligible to enroll in a Phase 3 long-term extension study in which patients received treatment with ULORIC for over three years.

In all three studies, patients received naproxen 250 mg twice daily or colchicine 0.6 mg once or twice daily for gout flare prophylaxis. In Study 1 the duration of prophylaxis was six months; in Study 2 and Study 3 the duration of prophylaxis was eight weeks.

The efficacy of ULORIC was also evaluated in a 4-week dose ranging study which randomized patients to: placebo, ULORIC 40 mg daily, ULORIC 80 mg daily, or ULORIC 120 mg daily. Patients who completed this study were eligible to enroll in a long-term extension study in which patients received treatment with ULORIC for up to five years.

Patients in these studies were representative of the patient population for which ULORIC use is intended. Table 2 summarizes the demographics and baseline characteristics for the patients enrolled in the studies.

Table 2: Patient Demographics and Baseline Characteristics in Study 1, Study 2, and Study 3
Male |  | 95%
Race: | Caucasian | 80%
 | African American | 10%
Ethnicity: Hispanic or Latino |  | 7%
Alcohol User |  | 67%
Mild to Moderate Renal Insufficiency (percent with estimated Clcr less than 90 mL/min) |  | 59%
History of Hypertension |  | 49%
History of Hyperlipidemia |  | 38%
BMI ≥30 kg/m^2 |  | 63%
Mean BMI |  | 33 kg/m^2
Baseline sUA ≥10 mg/dL |  | 36%
Mean baseline sUA |  | 9.7 mg/dL
Experienced a gout flare in previous year |  | 85%

Serum Uric Acid Level less than 6 mg/dL at Final Visit

ULORIC 80 mg was superior to allopurinol in lowering serum uric acid to less than 6 mg/dL at the final visit. ULORIC 40 mg daily, although not superior to allopurinol, was effective in lowering serum uric acid to less than 6 mg/dL at the final visit (Table 3).

Table 3: Proportion of Patients with Serum Uric Acid Levels less than 6 mg/dL at Final Visit
 |  |  |  |  | Difference in Proportion (95% CI)
Study [Randomization was balanced between treatment groups, except in Study 2 in which twice as many patients were randomized to each of the active treatment groups compared to placebo.] | ULORIC 40 mg daily | ULORIC 80 mg daily | allopurinol | Placebo | ULORIC 40 mg vs allopurinol | ULORIC 80 mg vs allopurinol
Study 1 (6 months) (N=2268) | 45% | 67% | 42% |  | 3% (-2%, 8%) | 25% (20%, 30%)
Study 2 (6 months) (N=643) |  | 72% | 39% | 1% |  | 33% (26%, 42%)
Study 3 (12 months) (N=491) |  | 74% | 36% |  |  | 38% (30%, 46%)

In 76% of ULORIC 80 mg patients, reduction in serum uric acid levels to less than 6 mg/dL was noted by the Week 2 visit. Average serum uric acid levels were maintained at 6 mg/dL or below throughout treatment in 83% of these patients.

In all treatment groups, fewer patients with higher baseline serum urate levels (≥10 mg/dL) and/or tophi achieved the goal of lowering serum uric acid to less than 6 mg/dL at the final visit; however, a higher proportion achieved a serum uric acid less than 6 mg/dL with ULORIC 80 mg than with ULORIC 40 mg or allopurinol.

Study 1 evaluated efficacy in patients with mild to moderate renal impairment (i.e., baseline estimated Clcr less than 90 mL/min). The results in this subgroup of patients are shown in Table 4.

Table 4: Proportion of Patients with Serum Uric Acid Levels less than 6 mg/dL in Patients with Mild or Moderate Renal Impairment at Final Visit
 |  |  | Difference in Proportion (95% CI)
ULORIC 40 mg daily (N=479) | ULORIC 80 mg daily (N=503) | allopurinol [Allopurinol patients (n=145) with estimated Clcr ≥30 mL/min and Clcr ≤59 mL/min were dosed at 200 mg daily.] 300 mg daily (N=501) | ULORIC 40 mg vs allopurinol | ULORIC 80 mg vs allopurinol
50% | 72% | 42% | 7% (1%, 14%) | 29% (23%, 35%)

14.2 Cardiovascular Safety Study

A randomized, double-blind, allopurinol-controlled CV outcomes study (CARES) was conducted to evaluate the CV risk of ULORIC (NCT01101035). The study compared the risk of MACE between patients treated with ULORIC (N=3098) and allopurinol-treated patients (N=3092). The primary endpoint was the time to first occurrence of a MACE defined as the composite of CV death, nonfatal MI, nonfatal stroke, or unstable angina with urgent coronary revascularization. The study was designed to exclude a prespecified risk margin of 1.3 for the hazard ratio of MACE. An independent committee conducted a blinded evaluation of serious CV adverse events according to predefined criteria (adjudication) for determination of MACE. The study was event driven and patients were followed until a sufficient number of primary outcome events accrued. The median on-study follow-up time was 2.6 years.

Patients randomized to ULORIC initially received 40 mg once daily which was increased to 80 mg once daily, if their sUA was ≥6mg/dL at Week 2. For patients randomized to allopurinol, those who had normal renal function or mild renal impairment (estimated creatinine clearance (eClcr) ≥60 to ˂90 mL/minute) initially received 300 mg once daily with 100 mg/day dose increments monthly until either sUA ˂6mg/dL or an allopurinol dosage of 600 mg once daily was achieved; those who had moderate renal impairment (eClcr ≥30 to ˂60 mL/minute) initially received 200 mg once daily with 100 mg/day dose increments monthly until either a sUA ˂6 mg/dL or an allopurinol dosage of 400 mg once daily was achieved.

The mean age of the population was 65 years (range: 44 to 93 years). Most patients were male (84%) and Caucasian (69%). Patients had a diagnosis of gout for approximately 12 years, a mean baseline sUA of 8.7 mg/dL, and 90% had experienced at least one gout flare in the past year. CV history included MI (39%), hospitalization for unstable angina (28%), cardiac revascularization (37%), and stroke (14%). The most prevalent comorbid conditions were hypertension (92%), hyperlipidemia (87%), diabetes mellitus (55%), diabetes mellitus with micro- or macrovascular disease (39%), and renal impairment [92% with an eClcr 30 to 89 mL/minute]. The use of CV disease medication was balanced across treatment groups. Baseline CV disease medications included: ACE inhibitors or ARBs (70%), lipid modifying agents (74%), aspirin (62%), beta-blockers (59%), calcium channel blockers (26%), and nonaspirin antiplatelet medications (31%).

Table 5 shows the study results for the primary MACE composite endpoint and its individual components. For the composite primary endpoint, the ULORIC group was non-inferior compared with the allopurinol group. The rates of nonfatal MI, stroke, and unstable angina with urgent coronary revascularization were similar. There was a higher rate of CV deaths in patients treated with ULORIC (134 CV deaths; 1.5 per 100 PY) than in allopurinol-treated patients (100 CV deaths; 1.1 per 100 PY). Sudden cardiac death was the most common cause of adjudicated CV deaths in the ULORIC group (83 of 3,098; 2.7%) as compared to the allopurinol group (56 of 3,092; 1.8%). The biological plausibility of CV death associated with ULORIC is unclear.

All-cause mortality was higher in the ULORIC group (243 deaths [7.8%]; 2.6 per 100 PY) than the allopurinol group (199 deaths [6.4%]; 2.2 per 100 PY) [Hazard Ratio: 1.22, 95% CI: 1.01, 1.47], due to a higher rate of CV deaths.

Table 5: Patients with MACE in CARES (Cardiovascular Outcomes Study in Patients with Gout)
 | ULORIC N=3098 |  | Allopurinol N=3092 |  | Hazard Ratio
 | Number of Patients with Event (%) | Rate per 100 PY [Patient Years (PY)] | Number of Patients with Event (%) | Rate per 100 PY | 95% CI
Composite of primary endpoint MACE | 335 (10.8) | 3.8 | 321 (10.4) | 3.7 | 1.03 (0.89, 1.21)
Cardiovascular Death | 134 (4.3) | 1.5 | 100 (3.2) | 1.1 | 1.34 (1.03, 1.73)
Nonfatal MI | 111 (3.6) | 1.2 | 118 (3.8) | 1.3 | 0.93 (0.72, 1.21)
Nonfatal stroke | 71 (2.3) | 0.8 | 70 (2.3) | 0.8 | 1.01 (0.73, 1.41)
Unstable angina with urgent coronary revascularization | 49 (1.6) | 0.5 | 56 (1.8) | 0.6 | 0.86 (0.59, 1.26)

16 HOW SUPPLIED/STORAGE AND HANDLING

ULORIC 40 mg tablets are light green to green in color, round, debossed with "TAP" on one side and "40" on the other side and supplied as:

NDC Number | Size
64764-918-11 | Hospital Unit Dose Pack of 100 Tablets
64764-918-30 | Bottle of 30 Tablets
64764-918-90 | Bottle of 90 Tablets
64764-918-18 | Bottle of 500 Tablets

ULORIC 80 mg tablets are light green to green in color, teardrop shaped, debossed with "TAP" on one side and "80" on the other side and supplied as:

NDC Number | Size
64764-677-11 | Hospital Unit Dose Pack of 100 Tablets
64764-677-30 | Bottle of 30 Tablets
64764-677-13 | Bottle of 100 Tablets
64764-677-19 | Bottle of 1000 Tablets

STORAGE AND HANDLING

Protect from light. Store at 25°C (77°F); excursions permitted to 15° to 30°C (59° to 86°F) [See USP Controlled Room Temperature].

17 PATIENT COUNSELING INFORMATION

Advise the patient to read the FDA-approved patient labeling (Medication Guide).

CV Death

Inform patients that gout patients with established CV disease treated with ULORIC had a higher rate of CV death compared to those treated with allopurinol in a CV outcomes study. Inform all patients of the higher rate of CV death with ULORIC compared to allopurinol. Alert all patients (those with and without CV disease) for the development of signs and symptoms of CV events and to seek medical care promptly should they occur [see Warnings and Precautions (5.1)].

Gout Flares

Inform patients that after initiation of ULORIC an increase in gout flares can occur and that is not reason to stop taking the medication. Instruct patients that it is recommended to initiate and continue gout prophylaxis therapy for six months while taking ULORIC [see Warnings and Precautions (5.2)].

Hepatic Effects

Inform patients that hepatic effects, including fatal ones, have occurred in patients treated with ULORIC. Instruct them to inform their healthcare provider if they experience liver injury symptoms [see Warnings and Precautions (5.3)].

Serious Skin Reactions

Inform patients that serious skin and hypersensitivity reactions have occurred in patients treated with ULORIC. Instruct patients to discontinue ULORIC if they develop symptoms of these reactions [see Warnings and Precautions (5.4)].

PATIENT INFORMATION

MEDICATION GUIDE
ULORIC (Ū–'lor–ik)
(febuxostat)
tablets, for oral use

Read the Medication Guide that comes with ULORIC before you start taking it and each time you get a refill. There may be new information. The Medication Guide does not take the place of talking with your doctor about your medical condition or your treatment.

What is the most important information that I should know about ULORIC?
ULORIC may cause serious side effects, including:
Heart-related deaths.
Call your doctor or get emergency medical help right away if you have any of the following symptoms, especially if they are new, worse, or worry you:

- chest pain
- shortness of breath or trouble breathing
- dizziness, fainting or feeling lightheaded
- rapid or irregular heartbeat

- numbness or weakness on one side of your body
- slurring of speech
- sudden blurry vision or sudden severe headache

What is ULORIC?
ULORIC is a prescription medicine called a xanthine oxidase (XO) inhibitor used to lower blood uric acid levels in adult patients with gout when allopurinol has not worked well enough or when allopurinol is not right for you.
ULORIC is not for use in people who do not have symptoms of high blood uric acid levels.
It is not known if ULORIC is safe and effective in children.

Who should not take ULORIC?
Do not take ULORIC if you:

- take azathioprine (Azasan, Imuran)
- take mercaptopurine (Purinethol, Purixan)

What should I tell my doctor before taking ULORIC?
Before taking ULORIC tell your doctor about all of your medical conditions, including if you:

- have taken allopurinol and what happened to you while you were taking it.
- have a history of heart disease or stroke.
- have liver or kidney problems.
- are pregnant or plan to become pregnant. It is not known if ULORIC will harm your unborn baby. Talk with your doctor if you are pregnant or plan to become pregnant.
- are breastfeeding or plan to breastfeed. It is not known if ULORIC passes into your breast milk. You and your doctor should decide if you should take ULORIC while breastfeeding.

Tell your doctor about all the medicines you take, including prescription and over-the-counter medicines, vitamins, and herbal supplements. ULORIC may affect the way other medicines work, and other medicines may affect how ULORIC works.
Know the medicines you take. Keep a list of them to show your doctor and pharmacist when you get a new medicine.

How should I take ULORIC?

- Take ULORIC exactly as your doctor tells you to take it.
- ULORIC can be taken with or without food.
- ULORIC can be taken with antacids.
- Your gout may get worse (flare) when you start taking ULORIC. Do not stop taking ULORIC because you have a flare.

Your doctor may do certain tests while you take ULORIC.

What are the possible side effects of ULORIC?
ULORIC may cause serious side effects, including:

- Heart problems. See "What is the most important information I should know about ULORIC?".
- Gout Flares. Gout flares can happen when you start taking ULORIC. Your doctor may give you other medicines to help prevent your gout flares.
- Liver problems. Liver problems can happen in people who take ULORIC. Your doctor may do blood tests to check how well your liver is working before and during your treatment with ULORIC. Tell your doctor if you get any of the following signs or symptoms of liver problems:

- fatigue
- loss of appetite for several days or longer
- pain, aching, or tenderness on the right side of your stomach-area

- dark or "tea-colored" urine
- your skin or the white part of your eyes turns yellow (jaundice)

- Severe skin and allergic reactions. Serious skin and allergic reactions that may affect different parts of the body such as your liver, kidneys, heart or lungs, can happen in people who take ULORIC. Call your doctor right away or get emergency medical help if you have any of the following symptoms:

- rash
- red and painful skin
- severe skin blisters
- peeling skin

- sores around the lips, eyes or mouth
- swollen face, lips, mouth, tongue or throat
- flu-like symptoms

The most common side effects of ULORIC include:

- abnormal liver function tests
- nausea

- joint pain
- rash

These are not all of the possible side effects of ULORIC.
Call your doctor for medical advice about side effects. You may report side effects to FDA at 1-800-FDA-1088.

How should I store ULORIC?

- Store ULORIC at room temperature.
- Keep ULORIC out of the light.

Keep ULORIC and all medicines out of the reach of children.

General information about the safe and effective use of ULORIC.
Medicines are sometimes prescribed for purposes other than those listed in a Medication Guide. Do not use ULORIC for a condition for which it was not prescribed. Do not give ULORIC to other people, even if they have the same symptoms that you have. It may harm them.
You can ask your doctor or pharmacist for information about ULORIC that is written for health professionals.

What are the ingredients in ULORIC?
Active ingredient: febuxostat
Inactive ingredients: lactose monohydrate, microcrystalline cellulose, hydroxypropyl cellulose, sodium croscarmellose, silicon dioxide, magnesium stearate, and Opadry II, green
Distributed by:
Takeda Pharmaceuticals America, Inc.
Lexington, MA 02421
ULORIC is a registered trademark of Teijin Limited registered in the U.S. Patent and Trademark Office and used under license by Takeda Pharmaceuticals America, Inc.
All other trademarks are the property of their respective owners.
©2009-2023 Takeda Pharmaceuticals America, Inc.
For more information, go to www.ULORIC.com or call 1-877-TAKEDA (1-877-825-3327).

This Medication Guide has been approved by the U.S. Food and Drug Administration

ULR015 R10

Revised: April 2023

541887-04

PRINCIPAL DISPLAY PANEL - 40 mg Tablet Bottle Label

NDC 64764-918-30
30 Tablets

Uloric
(febuxostat)
tablets

40 mg

Dispense the accompanying
Medication Guide to each patient.

PRINCIPAL DISPLAY PANEL - 80 mg Tablet Bottle Label

NDC 64764-677-30
30 Tablets

Uloric
(febuxostat)
tablets

80 mg

Dispense the accompanying
Medication Guide to each patient.